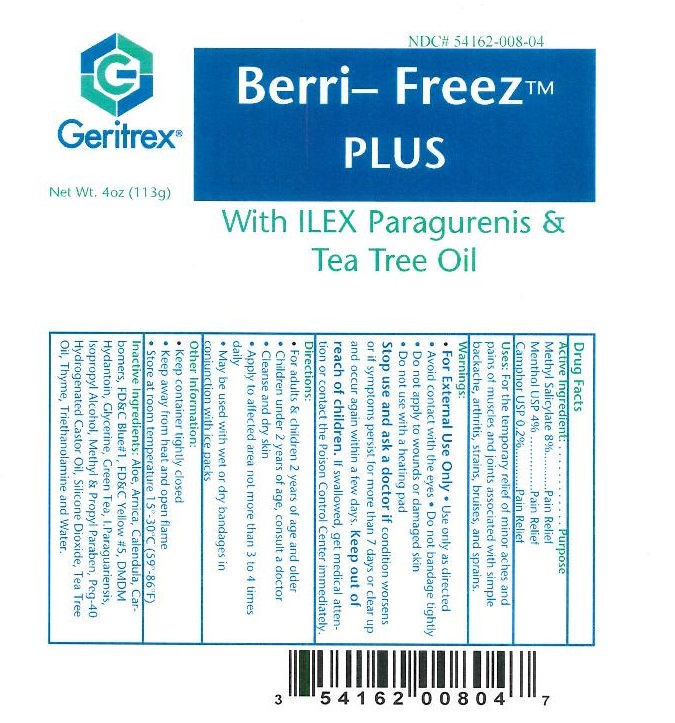 DRUG LABEL: Berri-Freez Plus
NDC: 54162-008 | Form: GEL
Manufacturer: Geritrex LLC
Category: otc | Type: HUMAN OTC DRUG LABEL
Date: 20120823

ACTIVE INGREDIENTS: MENTHOL 4.52 g/113 g; CAMPHOR (SYNTHETIC) 0.226 g/113 g; METHYL SALICYLATE 9.04 g/113 g
INACTIVE INGREDIENTS: CARBOMER HOMOPOLYMER TYPE C; ALOE VERA LEAF; ARNICA MONTANA; CALENDULA ARVENSIS LEAF; PEG-40 CASTOR OIL; FD&C BLUE NO. 1; FD&C YELLOW NO. 5; DMDM HYDANTOIN; GLYCERIN; ILEX PARAGUARIENSIS LEAF; ISOPROPYL ALCOHOL; METHYLPARABEN; PROPYLPARABEN; THYME; TRIETHANOLAMINE BENZOATE; WATER; GREEN TEA LEAF; SILICON DIOXIDE; TEA TREE OIL

Berri-Freez Plus

Drug Facts

Active Ingredient: . . . . . . . . . . . . Purpose

Methyl Salicylate 8% Pain Relief

Menthol USP 4% Pain Relief
Camphor USP 0.2% Pain Relief

Uses

For the temporary relief of minor aches and
pains of muscles and joints associated with simple
backache, arthritis, strains, bruises, and sprains.

WARNINGS

- For External Use Only
- Use only as directed
- Avoid contact with eyes
- Do not bandage tightly
- Do not apply to wounds or damaged skin
- Do not use with heating pad

Stop use and ask a doctor if condition worsens or if symptoms persist for more than 7 days or clear up and occur again within a few days.

Keep out of reach of children. If swallowed, get medical attention or contact the Poison Control Center immediately.

DOSAGE AND ADMINISTRATION

- Apply to affected area not more than 3 to 4 times daily

INDICATIONS AND USAGE

- For adults & children 2 years of age and older
- Children under 2 years of age, consult a doctor
- Cleanse and dry skin
- Apply to affected area not more than 3 to 4 times daily
- May be used with wet or dry bandages in conjunction with ice packs

STORAGE AND HANDLING

- Keep container tightly closed
- Keep away from heat and open flame
- Store at room temperature 15°-30°C (59°-86°F)

Inactive Ingredient

Aloe, Arnica, Calendula, Carbomers, FD&C Blue #1, FD&C Yellow #5, DMDM Hydantoin, Glycerine, Green Tea, L. Paraguariensis, Isopropyl Alcohol, Methyl & Propyl Paraben, PEG-40, Hydrogenated Castor Oil, Silicone Dioxide, Tea Tree Oil, Thyme, Triethanolamine, Water